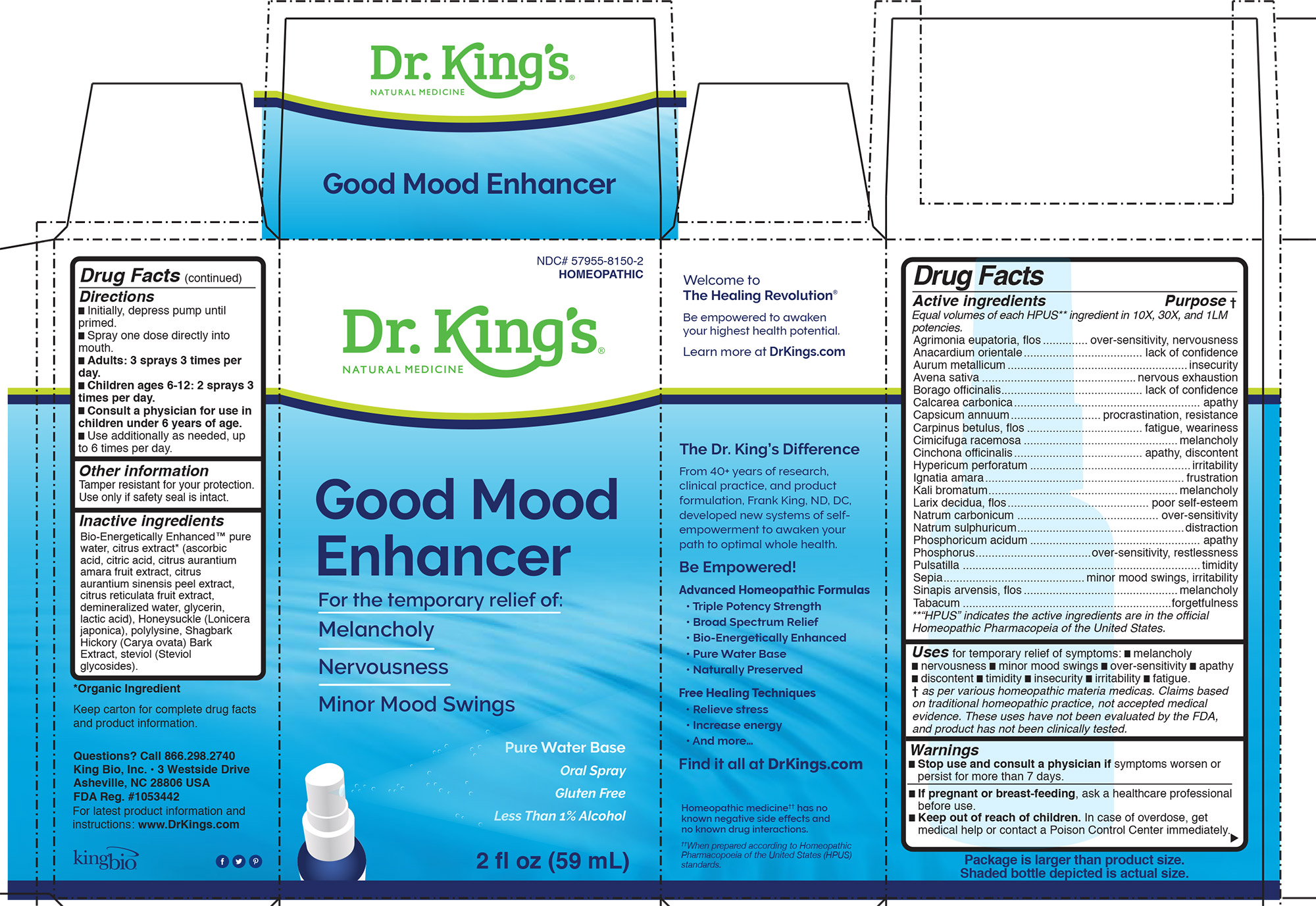 DRUG LABEL: Good Mood Enhancer
NDC: 57955-8150 | Form: LIQUID
Manufacturer: King Bio Inc.
Category: homeopathic | Type: HUMAN OTC DRUG LABEL
Date: 20200714

ACTIVE INGREDIENTS: SEMECARPUS ANACARDIUM JUICE 10 [hp_X]/59 mL; AGRIMONIA EUPATORIA FLOWER 10 [hp_X]/59 mL; GOLD 10 [hp_X]/59 mL; AVENA SATIVA FLOWERING TOP 10 [hp_X]/59 mL; BORAGE 10 [hp_X]/59 mL; OYSTER SHELL CALCIUM CARBONATE, CRUDE 10 [hp_X]/59 mL; CAPSICUM 10 [hp_X]/59 mL; CARPINUS BETULUS FLOWERING TOP 10 [hp_X]/59 mL; BLACK COHOSH 10 [hp_X]/59 mL; CINCHONA OFFICINALIS BARK 10 [hp_X]/59 mL; HYPERICUM PERFORATUM 10 [hp_X]/59 mL; STRYCHNOS IGNATII SEED 10 [hp_X]/59 mL; POTASSIUM BROMIDE 10 [hp_X]/59 mL; LARIX DECIDUA FLOWERING TOP 10 [hp_X]/59 mL; SODIUM CARBONATE 10 [hp_X]/59 mL; SODIUM SULFATE 10 [hp_X]/59 mL; PHOSPHORIC ACID 10 [hp_X]/59 mL; PHOSPHORUS 10 [hp_X]/59 mL; PULSATILLA VULGARIS 10 [hp_X]/59 mL; SEPIA OFFICINALIS JUICE 10 [hp_X]/59 mL; SINAPIS ARVENSIS FLOWERING/FRUITING TOP 10 [hp_X]/59 mL; TOBACCO LEAF 10 [hp_X]/59 mL
INACTIVE INGREDIENTS: WATER; CARYA OVATA BARK; CITRUS BIOFLAVONOIDS; LONICERA JAPONICA FLOWER; POLYEPSILON-LYSINE (4000 MW); REBAUDIOSIDE A

Good Mood Enhancer

HPUS Active Ingredients

Equal volumes of each ingredient in 10X, 30X, and LM1 potencies.

Agrimonia eupatoria, flos

Anacardium orientale

Aurum metallicum

Avena sativa

Borago officinalis

Calcarea carbonica

Capsicum annuum

Carpinus betulus, flos

Cimicifuga racemosa

Cinchona officinalis

Hypericum perforatum

Ignatia amara

Kali bromatum

Larix decidua, flos

Natrum carbonicum

Natrum sulphuricum

Phosphoricum acidum

Phosphorus

Pulsatilla

Sepia

Sinapis arvensis, flos

Tabacum

Inactive Ingredients

Bio-Energetically Enhanced™ pure
water, citrus extract* (ascorbic
acid, citric acid, citrus aurantium
amara fruit extract, citrus
aurantium sinensis peel extract,
citrus reticulata fruit extract,
demineralized water, glycerin,
lactic acid), Honeysuckle (Lonicera
japonica), polylysine, Shagbark
Hickory (Carya ovata) Bark
Extract, steviol (Steviol
glycosides)

Uses

for temporary relief of symptoms:

- melancholy
- nervousness
- minor mood swings
- over-sensitivity
- apathy
- discontent
- timidity
- insecurity
- irritability
- fatigue

Warnings

Stop use and consult a physician if symptoms worsen or
persist for more than 7 days.

PREGNANCY OR BREAST FEEDING

If pregnant or breast-feeding, ask a healthcare professional
before use.

Keep out of reach of children. In case of overdose, get
medical help or contact a Poison Control Center immediately

Directions

- Initially, depress pump until primed.
- Spray one dose directly into mouth.
- Adults: 3 sprays 3 times per day.
- Children ages 6-12: 2 sprays 3 times per day.
- Consult a physician for use in children under 6 years of age.
- Use additionally as needed, up to 6 times per day.

Active ingredients ................. Purpose

Equal volumes of each HPUS** ingredient in 10X, 30X, and 1LM
potencies.
Agrimonia eupatoria, flos.............. over-sensitivity, nervousness
Anacardium orientale..................................... lack of confidence
Aurum metallicum........................................................insecurity
Avena sativa ................................................nervous exhaustion
Borago officinalis............................................ lack of confidence
Calcarea carbonica.......................................................... apathy
Capsicum annuum............................ procrastination, resistance
Carpinus betulus, flos .................................... fatigue, weariness
Cimicifuga racemosa ................................................melancholy
Cinchona officinalis........................................ apathy, discontent
Hypericum perforatum ..................................................irritability
Ignatia amara.............................................................. frustration
Kali bromatum...........................................................melancholy
Larix decidua, flos............................................ poor self-esteem
Natrum carbonicum ............................................ over-sensitivity
Natrum sulphuricum....................................................distraction
Phosphoricum acidum ..................................................... apathy
Phosphorus....................................over-sensitivity, restlessness
Pulsatilla ..........................................................................timidity
Sepia............................................minor mood swings, irritability
Sinapis arvensis, flos................................................melancholy
Tabacum .................................................................forgetfulness
**“HPUS” indicates the active ingredients are in the official
Homeopathic Pharmacopeia of the United States.

Questions? Call 866.298.2740
King Bio, Inc. • 3 Westside Drive
Asheville, NC 28806 USA
FDA Reg. #1053442

For latest product information and
instructions: www.DrKings.com

Other information
Tamper resistant for your protection. Use only if safety seal is intact.